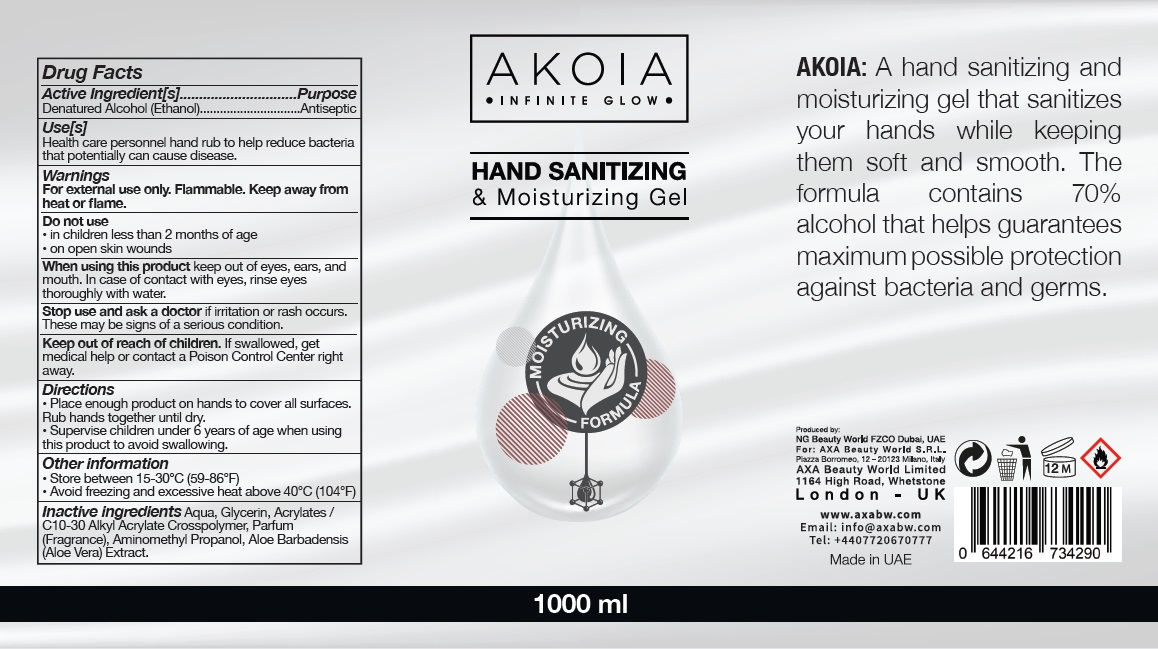 DRUG LABEL: Akoia Hand Sanitizer
NDC: 79919-001 | Form: GEL
Manufacturer: NG BEAUTY WORLD FZCO
Category: otc | Type: HUMAN OTC DRUG LABEL
Date: 20200807

ACTIVE INGREDIENTS: ALCOHOL 70 mL/100 mL
INACTIVE INGREDIENTS: WATER; GLYCERIN; CARBOMER INTERPOLYMER TYPE A (ALLYL SUCROSE CROSSLINKED); AMINOMETHYLPROPANOL; ALOE VERA LEAF

AKOIA HAND SANITIZING & Moisturizing Gel

Active Ingredient[s]

Denatured Alcohol (Ethanol)

Purpose

Antiseptic

Use[s]

Health care personnel hand rub to help reduce bacteria that potentially can cause disease.

Warnings

For external use only. Flammable. Keep away from heat or flame.

Do not use

• in children less than 2 months of age

• on open skin wounds

When using this product keep out of eyes, ears, and mouth. In case of contact with eyes, rinse eyes

thoroughly with water.

Stop use and ask a doctor if irritation or rash occurs. These may be signs of a serious condition.

Keep out of reach of children. If swallowed, get medical help or contact a Poison Control Center right away.

Directions

• Place enough product on hands to cover all surfaces. Rub hands together until dry.

• Supervise children under 6 years of age when using this product to avoid swallowing.

Other information

• Store between 15-30°C (59-86°F)

• Avoid freezing and excessive heat above 40°C (104°F)

INACTIVE INGREDIENT

Inactive ingredients Aqua, Glycerin, Acrylates /C10-30 Alkyl Acrylate Crosspolymer, Parfum (Fragrance),

Aminomethyl Propanol, Aloe Barbadensis (Aloe Vera) Extract.

• INFINITE GLOW •

HAND SANITIZING & Moisturizing Gel

MOISTURIZING FORMULA

AKOIA: A hand sanitizing and moisturizing gel that sanitizes your hands while keeping them soft

and smooth. The formula contains 70% alcohol that helps guarantees maximum possible protection

against bacteria and germs.

Produced by:

NG Beauty World FZCO Dubai, UAE

For: AXA Beauty World S.R.L.

Piazza Borromeo, 12 - 20123 Milano, Italy

AXA Beauty World Limited

1164 High Road, Whetstone

London - UK

www.axabw.com

Email: info@axabw.com

Tel: +4407720670777

Made in UAE